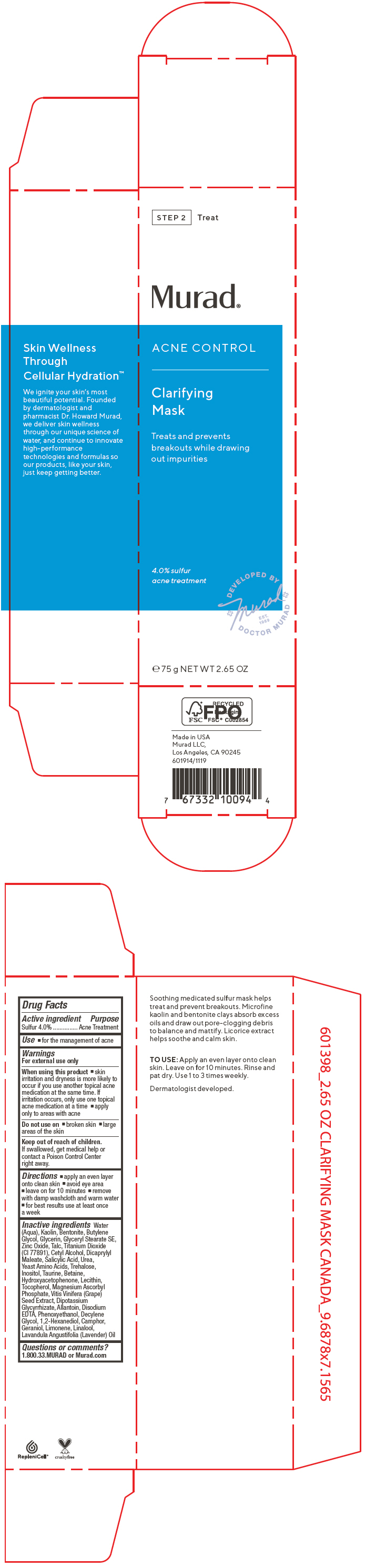 DRUG LABEL: Acne Control Clarifying Mask
NDC: 70381-115 | Form: CREAM
Manufacturer: Murad, LLC
Category: otc | Type: HUMAN OTC DRUG LABEL
Date: 20210702

ACTIVE INGREDIENTS: SULFUR 4 g/100 mL
INACTIVE INGREDIENTS: WATER; KAOLIN; BENTONITE; BUTYLENE GLYCOL; GLYCERIN; GLYCERYL STEARATE SE; ZINC OXIDE; TALC; TITANIUM DIOXIDE; CETYL ALCOHOL; DIOCTYL MALEATE; SALICYLIC ACID; UREA; AMINO ACIDS, SOURCE UNSPECIFIED; TREHALOSE; INOSITOL; TAURINE; BETAINE; HYDROXYACETOPHENONE; EGG PHOSPHOLIPIDS; TOCOPHEROL; MAGNESIUM ASCORBYL PHOSPHATE; VITIS VINIFERA SEED; GLYCYRRHIZINATE DIPOTASSIUM; ALLANTOIN; EDETATE DISODIUM ANHYDROUS; PHENOXYETHANOL; DECYLENE GLYCOL; 1,2-HEXANEDIOL; CAMPHOR (SYNTHETIC); GERANIOL; LIMONENE, (+)-; LINALOOL, (+/-)-; LAVENDER OIL

Acne Control Clarifying Mask

Drug Facts

Active ingredient

Sulfur 4.0%

Purpose

Acne Treatment

Use

- for the management of acne

Warnings

For external use only

When using this product

- skin irritation and dryness is more likely to occur if you use another topical acne medication at the same time. If irritation occurs, only use one topical acne medication at a time
- apply only to areas with acne

Do not use on

- broken skin
- large areas of the skin

Keep out of reach of children. If swallowed, get medical help or contact a Poison Control Center right away.

Directions

- apply an even layer onto clean skin
- avoid eye area
- leave on for 10 minutes
- remove with damp washcloth and warm water
- for best results use at least once a week

Inactive ingredients

Water (Aqua), Kaolin, Bentonite, Butylene Glycol, Glycerin, Glyceryl Stearate SE, Zinc Oxide, Talc, Titanium Dioxide (CI 77891), Cetyl Alcohol, Dicaprylyl Maleate, Salicylic Acid, Urea, Yeast Amino Acids, Trehalose, Inositol, Taurine, Betaine, Hydroxyacetophenone, Lecithin, Tocopherol, Magnesium Ascorbyl Phosphate, Vitis Vinifera (Grape) Seed Extract, Dipotassium Glycyrrhizate, Allantoin, Disodium EDTA, Phenoxyethanol, Decylene Glycol, 1,2-Hexanediol, Camphor, Geraniol, Limonene, Linalool, Lavandula Angustifolia (Lavender) Oil

Questions or comments?

1.800.33.MURAD or Murad.com

PRINCIPAL DISPLAY PANEL - 75 g Tube Carton

STEP 2
Treat

Murad®

ACNE CONTROL

Clarifying
Mask

Treats and prevents
breakouts while drawing
out impurities

4.0% sulfur
acne treatment

DEVELOPED BY
+ Murad +
EST.
1989
DOCTOR MURAD

℮ 75 g NET WT 2.65 OZ